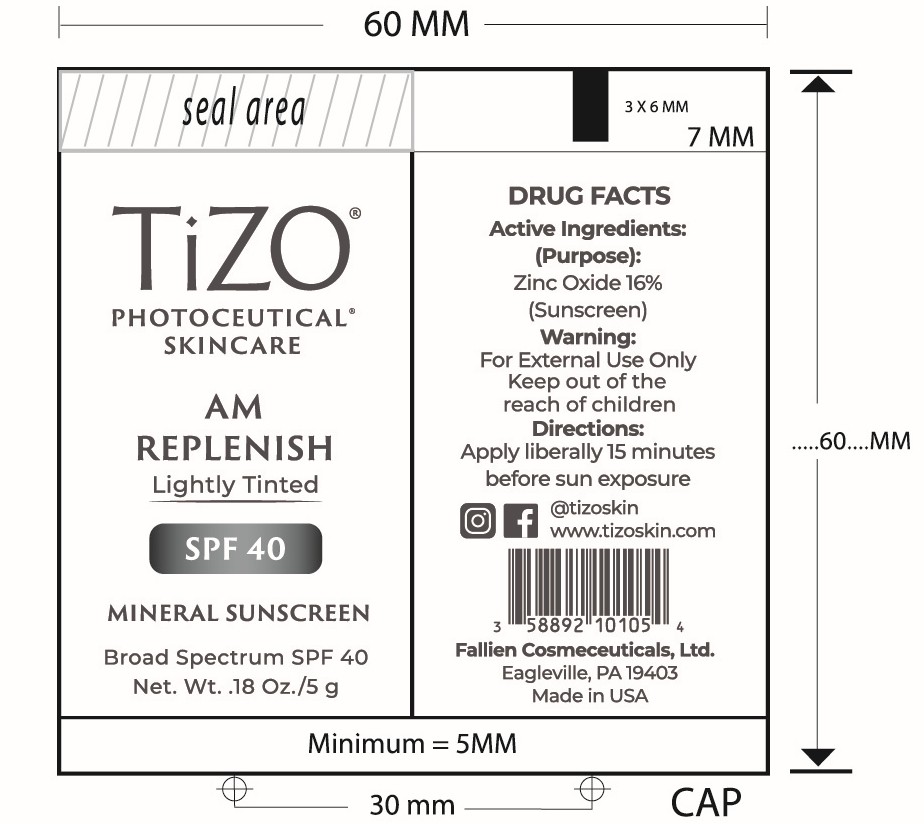 DRUG LABEL: TiZO Photoceutical AM Replenish - Tinted
NDC: 58892-101 | Form: CREAM
Manufacturer: Fallien Cosmeceuticals, LTD
Category: otc | Type: HUMAN OTC DRUG LABEL
Date: 20250128

ACTIVE INGREDIENTS: ZINC OXIDE 160 mg/1 g
INACTIVE INGREDIENTS: DIMETHICONE CROSSPOLYMER; HYDROGEN DIMETHICONE (20 CST); PEG-10 DIMETHICONE (600 CST); POLYHYDROXYSTEARIC ACID (2300 MW); CAPRYLIC/CAPRIC TRIGLYCERIDE; CERAMIDE 3; CYCLOHEXASILOXANE; DIMETHICONE; TETRAHEXYLDECYL ASCORBATE; DIMETHICONE/VINYL DIMETHICONE CROSSPOLYMER (SOFT PARTICLE); ALPHA-TOCOPHEROL ACETATE; VINYL DIMETHICONE/METHICONE SILSESQUIOXANE CROSSPOLYMER; DIMETHICONOL (2000 CST); IRON OXIDES; CYCLOPENTASILOXANE

Active Ingredient:

Zinc Oxide 16%

(Purpose)

Sunscreen

Directions:

Apply liberally 15 minutes before sun exposure.

Warning:

For external use only.

Warning and Directions:

For external use only. Appply liberally 15 minutes before sun exposure.

INACTIVE INGREDIENT

Capric/Caprylic Triglyceride, Ceramide 3, Cyclohexasiloxane, Cyclopentasiloxane, Dimethicone, Dimethicone Crosspolymer, Dimethicone/Vinyl Dimethicone Crosspolymer, Dimethiconol, Iron Oxide, Hydrogen Dimethicone, PEG-10 Dimethicone, Polyhydroxystearic Acid, Tetrahexyldecyl Ascorbate, Tocopheryl Acetate, Vinyl Dimethicone/Methicone Silsesquioxane Crosspolymer